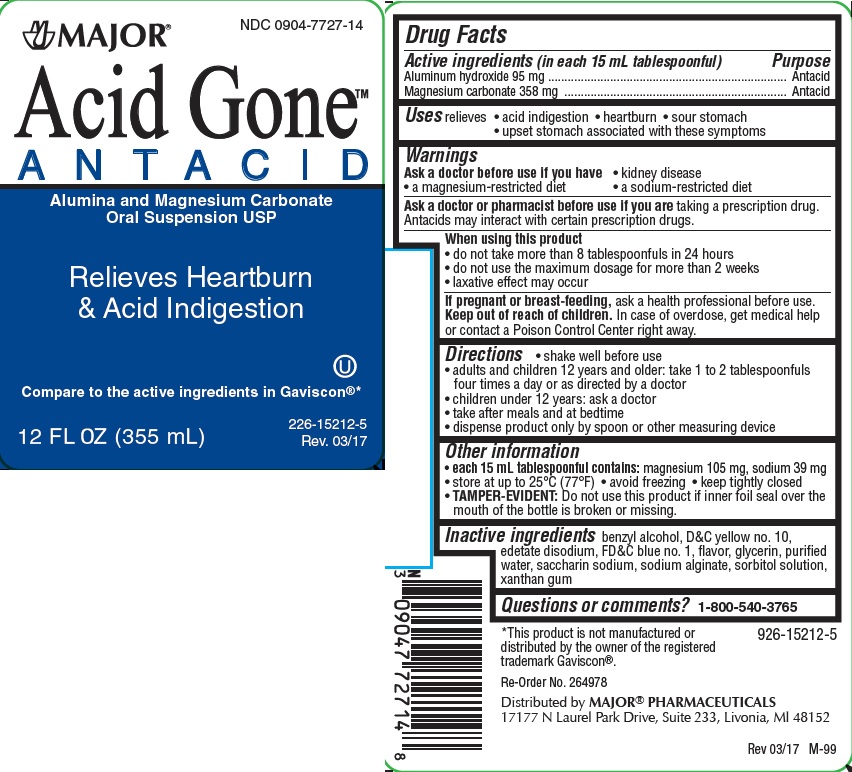 DRUG LABEL: ACID GONE ANTACID
NDC: 0904-7727 | Form: LIQUID
Manufacturer: Major Pharmaceuticals
Category: otc | Type: HUMAN OTC DRUG LABEL
Date: 20231102

ACTIVE INGREDIENTS: ALUMINUM HYDROXIDE 95 mg/15 mL; MAGNESIUM CARBONATE 358 mg/15 mL
INACTIVE INGREDIENTS: BENZYL ALCOHOL; D&C YELLOW NO. 10; EDETATE DISODIUM; FD&C BLUE NO. 1; GLYCERIN; SACCHARIN SODIUM; SODIUM ALGINATE; SORBITOL SOLUTION; WATER; XANTHAN GUM

MAJOR ACID GONE

Active ingredient (in each 15mL tablespoonful)

Aluminum hydroxide 95mg

Magnesium carbonate 358mg

Purpose

Antacid

Uses

relieves

- heartburn
- acid indigestion
- sour stomach
- upset stomach associated with these symptoms

Warnings

Ask a doctor before use if you have

- kidney disease
- a magnesium-restricted diet
- a sodium-restricted diet

Ask a doctor or pharmacist before use if you are taking a prescription drug.
Antacids may interact with certain prescription drugs.
When using this product

- do not take more than 8 tablespoonfuls in 24 hours
- do not use the maximum dosage for more than 2 weeks
- laxative effect may occur

If pregnant or breast-feeding, ask a health professional before use.

Keep out of reach of children.

In case of overdose, get medical help or contact a Poison Control Center right away.

Directions

- shake well before use
- adults and children 12 years and older: take 1 to 2 tablespoonfuls four times a day or as directed by a doctor
- children under 12 years: ask a doctor
- take after meals and at bedtime
- dispense product only by spoon or other measuring device

Other information

- each 15 mL tablespoonful contains: magnesium 105mg, sodium 39mg
- store at up to 25°C (77°F)
- avoid freezing
- keep tightly closed
- TAMPER-EVIDENT: Do not use this product if inner foil seal over the mouth of the bottle is broken or missing.

Inactive ingredients (Regular Strength)

benzyl alcohol, D&C yellow #10, edetate disodium, FD&C blue #1, flavor, glycerin, purified water, saccharin sodium, sodium alginate, sorbitol solution, xanthan gum

Questions or comments?

1-800-540-3765

Principal Display Panel

major

NDC 0904-7727-14

Acid Gone Antacid

Alumina and Magnesium Carbonate
Oral Suspension USP

Relieves Heartburn
& Acid Indigestion

Compare to the active ingredients in Gaviscon® *

12 FL OZ (355 mL)